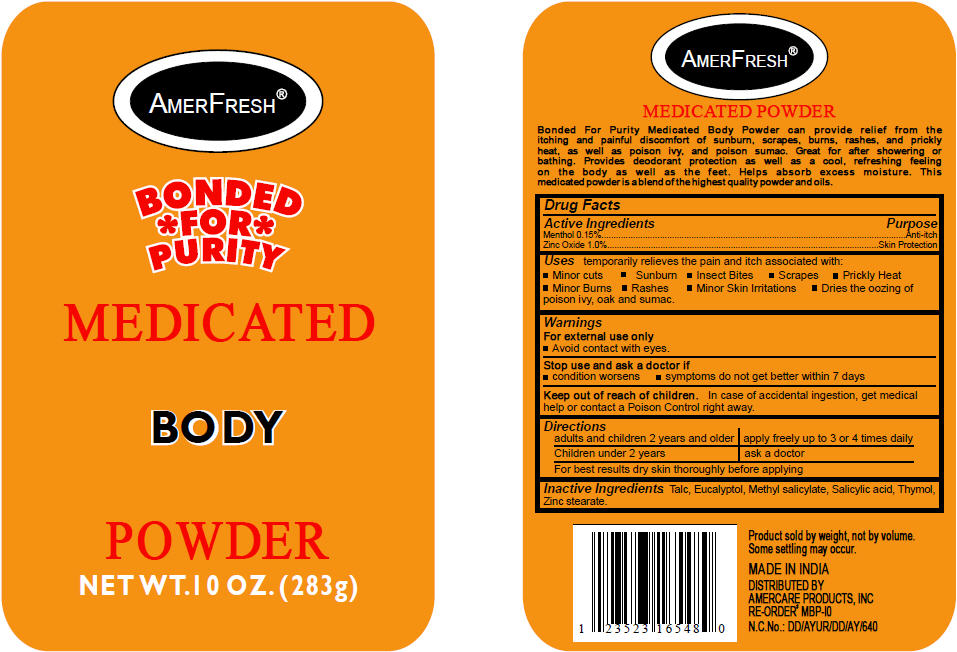 DRUG LABEL: Amerfresh Medicated
NDC: 51460-0504 | Form: POWDER
Manufacturer: Amercare Products Inc
Category: otc | Type: HUMAN OTC DRUG LABEL
Date: 20110512

ACTIVE INGREDIENTS: Menthol 0.15 g/100 g; Zinc Oxide 1 g/100 g
INACTIVE INGREDIENTS: Talc 97.4 g/100 g; Salicylic Acid; Methyl Salicylate; Eucalyptol; Thymol; Zinc Stearate

AMERFRESH®
MEDICATED
BODY
POWDER

Drug Facts

ACTIVE INGREDIENT

Active Ingredients | Purpose
Menthol 0.15% | Anti-itch
Zinc Oxide 1.0% | Skin Protection

Uses

temporarily relieves the pain and itch associated with:

- Minor cuts
- Sunburn
- Insect Bites
- Scrapes
- Prickly Heat
- Minor Burns
- Rashes
- Minor Skin Irritations
- Dries the oozing of poison ivy, oak and sumac.

Warnings

For external use only

WHEN USING

- Avoid contact with eyes.

Stop use and ask a doctor if

- condition worsens
- symptoms do not get better within 7 days

Keep out of reach of children. In case of accidental ingestion, get medical help or contact a Poison Control right away.

Directions

adults and children 2 years and older | apply freely up to 3 or 4 times daily
Children under 2 years | ask a doctor
For best results dry skin thoroughly before applying

Inactive Ingredients

Talc, Eucalyptol, Methyl salicylate, Salicylic acid, Thymol, Zinc stearate.

DISTRIBUTED BY
AMERCARE PRODUCTS, INC

PRINCIPAL DISPLAY PANEL - 283g Container Label

AMERFRESH®

BONDED
*FOR*
PURITY

MEDICATED

BODY

POWDER

NET WT.10 OZ. (283g)